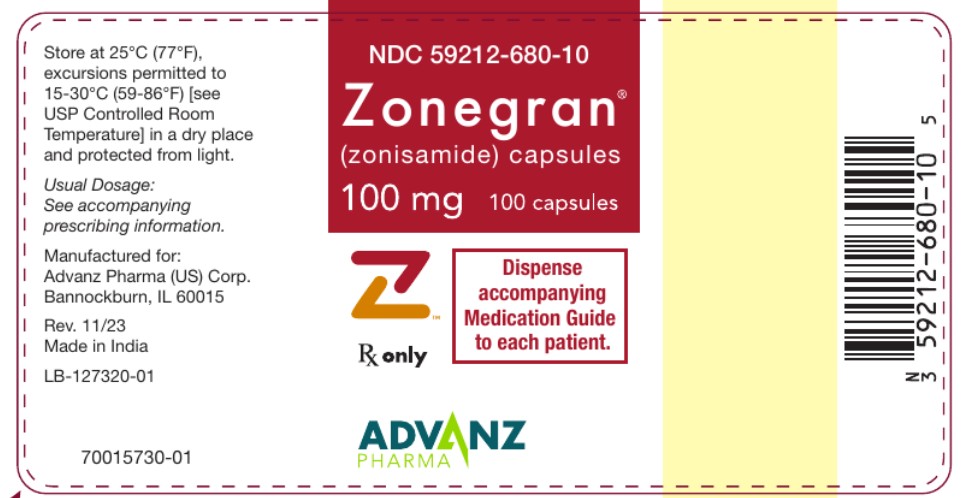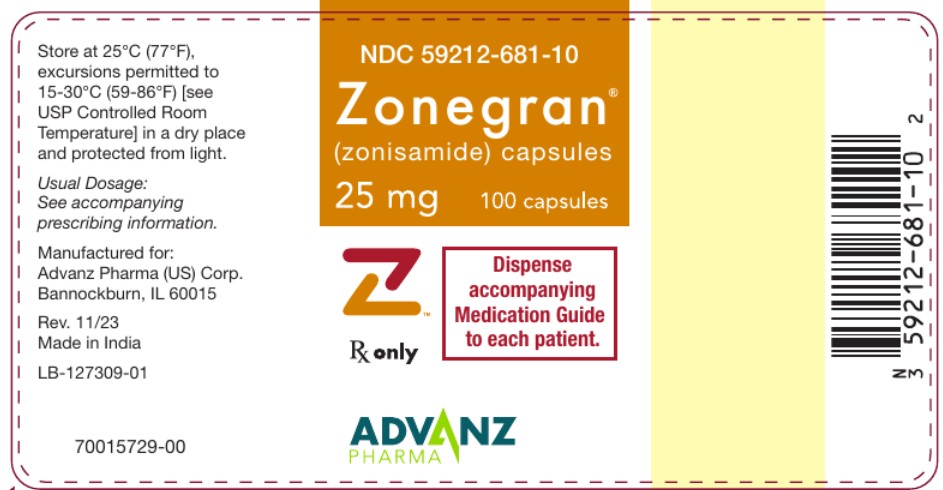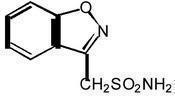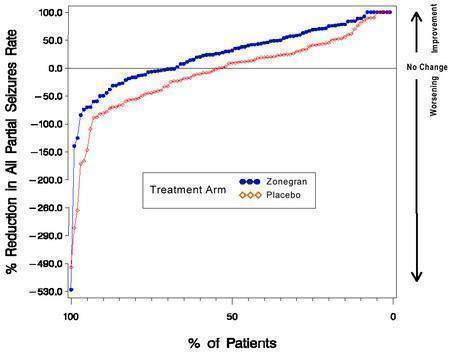 DRUG LABEL: Zonegran
NDC: 59212-681 | Form: CAPSULE
Manufacturer: Advanz Pharma (US) Corp.
Category: prescription | Type: Human Prescription Drug Label
Date: 20250912

ACTIVE INGREDIENTS: ZONISAMIDE 25 mg/1 1
INACTIVE INGREDIENTS: MICROCRYSTALLINE CELLULOSE; HYDROGENATED SOYBEAN OIL; SODIUM LAURYL SULFATE; GELATIN, UNSPECIFIED; TITANIUM DIOXIDE

ZONEGRAN® (zonisamide) capsules, for oral administration
Rx Only

DESCRIPTION

ZONEGRAN® (zonisamide) is an antiseizure drug chemically classified as a sulfonamide and unrelated to other antiseizure agents. The active ingredient is zonisamide, 1,2-benzisoxazole-3-methanesulfonamide. The empirical formula is C8H8N2O3S with a molecular weight of 212.23. Zonisamide is a white powder, pKa = 10.2, and is moderately soluble in water (0.80 mg/mL) and 0.1 N HCl (0.50 mg/mL).

The chemical structure is:

ZONEGRAN is supplied for oral administration as capsules containing 25 mg or 100 mg zonisamide.

Each 25 mg capsule contains the labeled amount of zonisamide plus the following inactive ingredients: microcrystalline cellulose, hydrogenated vegetable oil, sodium lauryl sulfate, gelatin, and titanium dioxide.

Each 100 mg capsule contains the labeled amount of zonisamide plus the following inactive ingredients: microcrystalline cellulose, hydrogenated vegetable oil, sodium lauryl sulfate, gelatin, titanium dioxide, FD&C Red No. 40 and FD&C Yellow No. 6.

CLINICAL PHARMACOLOGY

Mechanism of Action:

The precise mechanism(s) by which zonisamide exerts its antiseizure effect is unknown. Zonisamide demonstrated anticonvulsant activity in several experimental models. In animals, zonisamide was effective against tonic extension seizures induced by maximal electroshock but ineffective against clonic seizures induced by subcutaneous pentylenetetrazol. Zonisamide raised the threshold for generalized seizures in the kindled rat model and reduced the duration of cortical focal seizures induced by electrical stimulation of the visual cortex in cats. Furthermore, zonisamide suppressed both interictal spikes and the secondarily generalized seizures produced by cortical application of tungstic acid gel in rats or by cortical freezing in cats. The relevance of these models to human epilepsy is unknown.

Zonisamide may produce these effects through action at sodium and calcium channels. In vitro pharmacological studies suggest that zonisamide blocks sodium channels and reduces voltage-dependent, transient inward currents (T-type Ca^2+ currents), consequently stabilizing neuronal membranes and suppressing neuronal hypersynchronization. In vitro binding studies have demonstrated that zonisamide binds to the GABA/benzodiazepine receptor ionophore complex in an allosteric fashion which does not produce changes in chloride flux. Other in vitro studies have demonstrated that zonisamide (10–30 µg/mL) suppresses synaptically-driven electrical activity without affecting postsynaptic GABA or glutamate responses (cultured mouse spinal cord neurons) or neuronal or glial uptake of [^3H]-GABA (rat hippocampal slices). Thus, zonisamide does not appear to potentiate the synaptic activity of GABA. In vivo microdialysis studies demonstrated that zonisamide facilitates both dopaminergic and serotonergic neurotransmission.

Zonisamide is a carbonic anhydrase inhibitor. The contribution of this pharmacological action to the therapeutic effects of zonisamide is unknown. However, as a carbonic anhydrase inhibitor, zonisamide may cause metabolic acidosis (see WARNINGS, Metabolic Acidosis subsection).

Pharmacokinetics:

Absorption

Following a 200-400 mg oral zonisamide dose, peak plasma concentrations (range: 2-5 µg/mL) in normal volunteers occur within 2-6 hours. In the presence of food, the time to maximum concentration is delayed, occurring at 4-6 hours, but food has no effect on the bioavailability of zonisamide. Zonisamide absorption is dose-proportional in the range of 200-400 mg. Cmax and AUC, however, increase disproportionately at 800 mg, possibly due to saturable binding of zonisamide to red blood cells. Once a stable dose is reached, steady state is achieved within 14 days.

Distribution

The apparent volume of distribution (V/F) of zonisamide is about 1.45 L/kg following a 400 mg oral dose. Zonisamide, at concentrations of 1.0–7.0 µg/mL, is approximately 40% bound to human plasma proteins. Zonisamide extensively binds to erythrocytes, resulting in an eight-fold higher concentration of zonisamide in red blood cells than in plasma. Protein binding of zonisamide is unaffected in the presence of therapeutic concentrations of phenytoin, phenobarbital or carbamazepine.

Metabolism and Elimination

Following oral administration of ^14C-zonisamide to healthy volunteers, only zonisamide was detected in plasma. Zonisamide is excreted primarily in urine as parent drug and as the glucuronide of a metabolite. Following multiple dosing, 62% of the radiolabeled dose was recovered in the urine, with 3% in the feces by day 10. Zonisamide undergoes acetylation by N-acetyl-transferases to form N-acetyl zonisamide and reduction to form the open ring metabolite, 2–sulfamoylacetyl phenol (SMAP). Of the excreted dose, 35% was recovered as zonisamide, 15% as N-acetyl zonisamide, and 50% as the glucuronide of SMAP. Reduction of zonisamide to SMAP is mediated by cytochrome P450 isozyme 3A4 (CYP3A4). Zonisamide does not induce its own metabolism. The plasma clearance of oral zonisamide is approximately 0.30–0.35 mL/min/kg in patients not receiving enzyme-inducing antiepilepsy drugs (AEDs). The clearance of zonisamide is increased to 0.5 mL/min/kg in patients concurrently on enzyme-inducing AEDs.

After a single-dose administration, renal clearance of zonisamide is approximately 3.5 mL/min. The clearance of an oral dose of zonisamide from red blood cells is 2 mL/min. The elimination half-life of zonisamide in plasma is approximately 63 hours. The elimination half-life of zonisamide in red blood cells is approximately 105 hours.

Specific Populations:

Renal Impairment: Single 300 mg zonisamide doses were administered to three groups of volunteers. Group 1 was a healthy group with a creatinine clearance ranging from 70–152 mL/min. Group 2 and Group 3 had creatinine clearances ranging from 14.5–59 mL/min and 10–20 mL/min, respectively. Zonisamide renal clearance decreased with decreasing renal function (3.42, 2.50, 2.23 mL/min, respectively). Marked renal impairment (creatinine clearance < 20 mL/min) was associated with an increase in zonisamide AUC of 35% (see DOSAGE AND ADMINISTRATION section).

Hepatic Impairment: The pharmacokinetics of zonisamide in patients with impaired liver function have not been studied (see DOSAGE AND ADMINISTRATION section).

Age: The pharmacokinetics of a 300 mg single dose of zonisamide was similar in young (mean age 28 years) and elderly subjects (mean age 69 years).

Gender and Race: Information on the effect of gender and race on the pharmacokinetics of zonisamide is not available.

Effects of ZONEGRAN on cytochrome P450 enzymes

In vitro studies using human liver microsomes show insignificant (<25%) inhibition of cytochrome P450 isozymes 1A2, 2A6, 2C9, 2C19, 2D6, 2E1, 3A4, 2B6 or 2C8 at zonisamide levels approximately two-fold or greater than clinically relevant unbound serum concentrations. Therefore, ZONEGRAN is not expected to affect the pharmacokinetics of other drugs via cytochrome P450-mediated mechanisms.

Potential for ZONEGRAN to affect other drugs

Anti-epileptic drugs

In epileptic patients, steady state dosing with ZONEGRAN resulted in no clinically relevant pharmacokinetic effects on carbamazepine, lamotrigine, phenytoin, or sodium valproate.

Oral contraceptives

In healthy subjects, steady state dosing with ZONEGRAN did not affect serum concentrations of ethinylestradiol or norethisterone in a combined oral contraceptive.

CYP2D6 substrates

Coadministration of multiple dosing of zonisamide up to 400 mg/day with single 50-mg doses of desipramine did not significantly affect the pharmacokinetic parameters of desipramine, a probe drug for CYP2D6 activity.

P-gp substrate
An in vitro study showed that zonisamide is a weak inhibitor of P-gp (MDR1) with an IC50 of 267 µmol/L. There is a theoretical potential for zonisamide to affect the pharmacokinetics of drugs which are P-gp substrates.

Caution is advised when starting or stopping ZONEGRAN or changing the ZONEGRAN dose in patients who are also receiving drugs which are P-gp substrates (e.g., digoxin, quinidine)

Potential for Medicinal Products to Affect ZONEGRAN

Concomitant medications that can induce or inhibit CYP3A4 or N-acetyl-transferases may affect the pharmacokinetics of zonisamide. Drugs which inhibit or induce glucuronide conjugation are not expected to influence the pharmacokinetics of zonisamide.

The absence of a clinically significant pharmacokinetic interaction between zonisamide and lamotrigine indicates a low potential for zonisamide to interact with substances which are metabolized by UDP-GT.

CYP3A4 Induction: Drugs that induce liver enzymes increase the metabolism and clearance of zonisamide and decrease its half-life. The half-life of zonisamide following a 400 mg dose in patients concurrently on enzyme-inducing AEDs such as phenytoin, carbamazepine, or phenobarbital was between 27-38 hours; the half-life of zonisamide in patients concurrently on the non-enzyme inducing AED, valproate, was 46 hours.

These effects are unlikely to be of clinical significance when ZONEGRAN is added to existing therapy; however, changes in zonisamide concentrations may occur if concomitant CYP3A4 inducing anti-epileptic or other drugs are withdrawn, dose adjusted or introduced, an adjustment of the ZONEGRAN dose may be required. If co-administration with a potent CYP3A4 inducer (e.g., rifampicin) is necessary, the patient should be closely monitored and the dose of ZONEGRAN and other drugs that are CYP3A4 substrate may need to be adjusted.

CYP3A4 Inhibition: Steady-state dosing of either ketoconazole (400 mg/day) or cimetidine (1200 mg/day) had no clinically relevant effects on the single dose pharmacokinetics of zonisamide given to healthy subjects. Therefore, modification of ZONEGRAN dosing is not necessary when co-administered with known CYP3A4 inhibitors.

Interactions of Zonisamide with Other Carbonic Anhydrase Inhibitors:

Concomitant use of ZONEGRAN, a carbonic anhydrase inhibitor, with any other carbonic anhydrase inhibitor (e.g., topiramate, acetazolamide or dichlorphenamide), may increase the severity of metabolic acidosis and may also increase the risks of hyperammonemia and kidney stone formation. Therefore, if ZONEGRAN is given concomitantly with another carbonic anhydrase inhibitor, the patient should be monitored for the appearance or worsening of metabolic acidosis (see WARNINGS, Metabolic Acidosis subsection and Hyperammonemia and Encephalopathy subsection and PRECAUTIONS, Drug Interactions subsection).

Clinical Studies:

The effectiveness of ZONEGRAN as adjunctive therapy (added to other antiepilepsy drugs) has been established in three multicenter, placebo-controlled, double blind, 3-month clinical trials (two domestic, one European) in 499 patients with refractory partial onset seizures with or without secondary generalization. Each patient had a history of at least four partial onset seizures per month in spite of receiving one or two antiepilepsy drugs at therapeutic concentrations. The 499 patients (209 women, 290 men) ranged in age from 13–68 years with a mean age of about 35 years. In the two US studies, over 80% of patients were Caucasian; 100% of patients in the European study were Caucasian. ZONEGRAN or placebo was added to the existing therapy. The primary measure of effectiveness was median percent reduction from baseline in partial seizure frequency. The secondary measure was proportion of patients achieving a 50% or greater seizure reduction from baseline (responders). The results described below are for all partial seizures in the intent-to-treat populations.

In the first study (n = 203), all patients had a 1-month baseline observation period, then received placebo or ZONEGRAN in one of two dose escalation regimens; either 1) 100 mg/day for five weeks, 200 mg/day for one week, 300 mg/day for one week, and then 400 mg/day for five weeks; or 2) 100 mg/day for one week, followed by 200 mg/day for five weeks, then 300 mg/day for one week, then 400 mg/day for five weeks. This design allowed a 100 mg vs. placebo comparison over weeks 1–5, and a 200 mg vs. placebo comparison over weeks 2–6; the primary comparison was 400 mg (both escalation groups combined) vs. placebo over weeks 8–12. The total daily dose was given as twice a day dosing. Statistically significant treatment differences favoring ZONEGRAN were seen for doses of 100, 200, and 400 mg/day.

In the second (n = 152) and third (n = 138) studies, patients had a 2–3 month baseline, then were randomly assigned to placebo or ZONEGRAN for three months. ZONEGRAN was introduced by administering 100 mg/day for the first week, 200 mg/day the second week, then 400 mg/day for two weeks, after which the dose (ZONEGRAN or placebo) could be adjusted as necessary to a maximum dose of 20 mg/kg/day or a maximum plasma level of 40 µg/mL. In the second study, the total daily dose was given as twice a day dosing; in the third study, it was given as a single daily dose. The average final maintenance doses received in the studies were 530 and 430 mg/day in the second and third studies, respectively. Both studies demonstrated statistically significant differences favoring ZONEGRAN for doses of 400–600 mg/day, and there was no apparent difference between once daily and twice daily dosing (in different studies). Analysis of the data (first 4 weeks) during titration demonstrated statistically significant differences favoring ZONEGRAN at doses between 100 and 400 mg/day. The primary comparison in both trials was for any dose over Weeks 5–12.

Table 1. Median % Reduction in All Partial Seizures and % Responders in Primary Efficacy Analyses: Intent-To-Treat Analysis
Study | Median % reduction in partial seizures |  | % Responders
 | ZONEGRAN | Placebo | ZONEGRAN | Placebo
Study 1: | n=98 | n=72 | n=98 | n=72
Weeks 8-12: | 40.5%* | 9.0% | 41.8%* | 22.2%
Study 2: | n=69 | n=72 | n=69 | n=72
Weeks 5-12: | 29.6%* | -3.2% | 29.0% | 15.0%
Study 3: | n=67 | n=66 | n=67 | n=66
Weeks 5-12: | 27.2%* | -1.1% | 28.0%* | 12.0%

* p<0.05 compared to placebo

Table 2. Median % Reduction in All Partial Seizures and % Responders for Dose Analyses in Study 1: Intent-To-Treat Analysis
Dose Group | Median % reduction in partial seizures |  | % Responders
 | ZONEGRAN | Placebo | ZONEGRAN | Placebo
100-400 mg/day: | n=112 | n=83 | n=112 | n=83
Weeks 1-12: | 32.3%* | 5.6% | 32.1%* | 9.6%
100 mg/day: | n=56 | n=80 | n=56 | n=80
Weeks 1-5: | 24.7%* | 8.3% | 25.0%* | 11.3%
200 mg/day: | n=55 | n=82 | n=55 | n=82
Weeks 2-6: | 20.4%* | 4.0% | 25.5%* | 9.8%

* p<0.05 compared to placebo

Figure 1 presents the proportion of patients (X-axis) whose percentage reduction from baseline in the all partial seizure rate was at least as great as that indicated on the Y-axis in the second and third placebo-controlled trials. A positive value on the Y-axis indicates an improvement from baseline (i.e., a decrease in seizure rate), while a negative value indicates a worsening from baseline (i.e., an increase in seizure rate). Thus, in a display of this type, the curve for an effective treatment is shifted to the left of the curve for placebo. The proportion of patients achieving any particular level of reduction in seizure rate was consistently higher for the ZONEGRAN groups compared to the placebo groups. For example, Figure 1 indicates that approximately 27% of patients treated with ZONEGRAN experienced a 75% or greater reduction, compared to approximately 12% in the placebo groups.

Figure 1 Proportion of Patients Achieving Differing Levels of Seizure Reduction in ZONEGRAN and Placebo Groups in Studies 2 and 3

No differences in efficacy based on age, sex or race, as measured by a change in seizure frequency from baseline, were detected.

INDICATIONS AND USAGE

ZONEGRAN is indicated as adjunctive therapy in the treatment of partial seizures in adults with epilepsy.

CONTRAINDICATIONS

ZONEGRAN is contraindicated in patients who have demonstrated hypersensitivity to sulfonamides or zonisamide.

WARNINGS

Potentially Fatal Reactions to Sulfonamides: Fatalities have occurred, although rarely, as a result of severe reactions to sulfonamides (zonisamide is a sulfonamide) including Stevens-Johnson syndrome, toxic epidermal necrolysis, fulminant hepatic necrosis, agranulocytosis, aplastic anemia, and other blood dyscrasias. Such reactions may occur when a sulfonamide is readministered irrespective of the route of administration. If signs of hypersensitivity or other serious reactions occur, discontinue zonisamide immediately. Specific experience with sulfonamide-type adverse reaction to zonisamide is described below.

Serious Skin Reactions:
Consideration should be given to discontinuing ZONEGRAN in patients who develop an otherwise unexplained rash. If the drug is not discontinued, patients should be observed frequently. Seven deaths from severe rash [i.e., Stevens-Johnson syndrome (SJS) and toxic epidermal necrolysis (TEN)] were reported in the first 11 years of marketing in Japan. All of the patients were receiving other drugs in addition to zonisamide. In post-marketing experience from Japan, a total of 49 cases of SJS or TEN have been reported, a reporting rate of 46 per million patient-years of exposure. Although this rate is greater than background, it is probably an underestimate of the true incidence because of under-reporting. There were no confirmed cases of SJS or TEN in the US, European, or Japanese development programs.

In the US and European randomized controlled trials, 6 of 269 (2.2%) zonisamide patients discontinued treatment because of rash compared to none on placebo. Across all trials during the US and European development, rash that led to discontinuation of zonisamide was reported in 1.4% of patients (12.0 events per 1000 patient-years of exposure). During Japanese development, serious rash or rash that led to study drug discontinuation was reported in 2.0% of patients (27.8 events per 1000 patient-years). Rash usually occurred early in treatment, with 85% reported within 16 weeks in the US and European studies and 90% reported within two weeks in the Japanese studies. There was no apparent relationship of dose to the occurrence of rash.

Serious Hematologic Events:
Two confirmed cases of aplastic anemia and one confirmed case of agranulocytosis were reported in the first 11 years of marketing in Japan, rates greater than generally accepted background rates. There were no cases of aplastic anemia and two confirmed cases of agranulocytosis in the US, European, or Japanese development programs. There is inadequate information to assess the relationship, if any, between dose and duration of treatment and these events.

Drug Reaction with Eosinophilia and Systemic Symptoms (DRESS)/Multi-Organ Hypersensitivity:
Drug Reaction with Eosinophilia and Systemic Symptoms (DRESS), also known as multi-organ hypersensitivity, has occurred with ZONEGRAN. Some of these events have been fatal or life-threatening. DRESS typically, although not exclusively, presents with fever, rash, lymphadenopathy and/or facial swelling, in association with other organ system involvement, such as hepatitis, nephritis, hematologic abnormalities, myocarditis, or myositis, sometimes resembling an acute viral infection. Eosinophilia is often present. This disorder is variable in its expression, and other organ systems not noted here may be involved. It is important to note that early manifestations of hypersensitivity (e.g., fever, lymphadenopathy) may be present even though rash is not evident. If such signs or symptoms are present, the patient should be evaluated immediately. ZONEGRAN should be discontinued if an alternative etiology for the signs or symptoms cannot be established.

Oligohidrosis and Hyperthermia in Pediatric Patients:

Oligohidrosis, sometimes resulting in heat stroke and hospitalization, is seen in association with zonisamide in pediatric patients.

During the pre-approval development program in Japan, one case of oligohidrosis was reported in 403 pediatric patients, an incidence of 1 case per 285 patient-years of exposure. While there were no cases reported in the US or European development programs, fewer than 100 pediatric patients participated in these trials.

In the first 11 years of marketing in Japan, 38 cases were reported, an estimated reporting rate of about 1 case per 10,000 patient-years of exposure. In the first year of marketing in the US, 2 cases were reported, an estimated reporting rate of about 12 cases per 10,000 patient-years of exposure. These rates are underestimates of the true incidence because of under-reporting. There has also been one report of heat stroke in an 18-year-old patient in the US.

Decreased sweating and an elevation in body temperature above normal characterized these cases. Many cases were reported after exposure to elevated environmental temperatures. Heat stroke, requiring hospitalization, was diagnosed in some cases. There have been no reported deaths.

Pediatric patients appear to be at an increased risk for zonisamide-associated oligohidrosis and hyperthermia. Patients, especially pediatric patients, treated with ZONEGRAN should be monitored closely for evidence of decreased sweating and increased body temperature, especially in warm or hot weather. Caution should be used when zonisamide is prescribed with other drugs that predispose patients to heat-related disorders; these drugs include, but are not limited to, carbonic anhydrase inhibitors and drugs with anticholinergic activity.

The practitioner should be aware that the safety and effectiveness of zonisamide in pediatric patients have not been established, and that zonisamide is not approved for use in pediatric patients.

Acute myopia and secondary angle closure glaucoma have been reported in patients receiving ZONEGRAN. Elevated intraocular pressure can lead to serious sequelae, including permanent vision loss, if left untreated.
Symptoms in reported cases have included acute onset of decreased visual acuity and/or ocular pain. Ophthalmologic findings can include myopia, anterior chamber shallowing, ocular hyperemia (redness), and increased intraocular pressure. Mydriasis may or may not be present. This syndrome may be associated with ciliochoroidal effusion resulting in anterior displacement of the lens and iris, with secondary angle closure glaucoma. Symptoms typically occur within one month after initiating ZONEGRAN therapy.
In contrast to primary narrow angle glaucoma, which is rare under 40 years of age, secondary angle closure glaucoma associated with ZONEGRAN has been reported both in pediatric patients and in adults. The primary treatment to reverse symptoms is discontinuation of ZONEGRAN as rapidly as possible, according to the judgment of the treating physician. Other therapeutic measures, in conjunction with discontinuation of ZONEGRAN, may be helpful. Myopia and secondary angle closure glaucoma usually resolve or improve after discontinuation of ZONEGRAN.

Suicidal Behavior and Ideation:

Antiepileptic drugs (AEDs), including ZONEGRAN, increase the risk of suicidal thoughts or behavior in patients taking these drugs for any indication. Patients treated with any AED for any indication should be monitored for the emergence or worsening of depression, suicidal thoughts or behavior, and/or any unusual changes in mood or behavior.

Pooled analyses of 199 placebo-controlled clinical trials (mono- and adjunctive therapy) of 11 different AEDs showed that patients randomized to one of the AEDs had approximately twice the risk (adjusted Relative Risk 1.8, 95% CI:1.2, 2.7) of suicidal thinking or behavior compared to patients randomized to placebo. In these trials, which had a median treatment duration of 12 weeks, the estimated incidence rate of suicidal behavior or ideation among 27,863 AED-treated patients was 0.43%, compared to 0.24% among 16,029 placebo-treated patients, representing an increase of approximately one case of suicidal thinking or behavior for every 530 patients treated. There were four suicides in drug-treated patients in the trials and none in placebo-treated patients, but the number is too small to allow any conclusion about drug effect on suicide.

The increased risk of suicidal thoughts or behavior with AEDs was observed as early as one week after starting drug treatment with AEDs and persisted for the duration of treatment assessed. Because most trials included in the analysis did not extend beyond 24 weeks, the risk of suicidal thoughts or behavior beyond 24 weeks could not be assessed.

The risk of suicidal thoughts or behavior was generally consistent among drugs in the data analyzed. The finding of increased risk with AEDs of varying mechanisms of action and across a range of indications suggests that the risk applies to all AEDs used for any indication. The risk did not vary substantially by age (5-100 years) in the clinical trials analyzed.

Table 3 shows absolute and relative risk by indication for all evaluated AEDs.

Table 3. Risk by Indication for Antiepileptic Drugs in the Pooled Analysis
Indication | Placebo Patients with Events Per 1000 Patients | Drug Patients with Events Per 1000 Patients | Relative Risk: Incidence of Events in Drug Patients/Incidence in Placebo Patients | Risk Difference: Additional Drug Patients with Events Per 1000 Patients
Epilepsy | 1.0 | 3.4 | 3.5 | 2.4
Psychiatric | 5.7 | 8.5 | 1.5 | 2.9
Other | 1.0 | 1.8 | 1.9 | 0.9
Total | 2.4 | 4.3 | 1.8 | 1.9

The relative risk for suicidal thoughts or behavior was higher in clinical trials for epilepsy than in clinical trials for psychiatric or other conditions, but the absolute risk differences were similar for the epilepsy and psychiatric indications.

Anyone considering prescribing ZONEGRAN or any other AED must balance the risk of suicidal thoughts or behavior with the risk of untreated illness. Epilepsy and many other illnesses for which AEDs are prescribed are themselves associated with morbidity and mortality and an increased risk of suicidal thoughts and behavior. Should suicidal thoughts and behavior emerge during treatment, the prescriber needs to consider whether the emergence of these symptoms in any given patient may be related to the illness being treated.

Patients, their caregivers, and families should be informed that AEDs increase the risk of suicidal thoughts and behavior and should be advised of the need to be alert for the emergence or worsening of the signs and symptoms of depression, any unusual changes in mood or behavior, or the emergence of suicidal thoughts, behavior, or thoughts about self-harm. Behaviors of concern should be reported immediately to healthcare providers (see WARNINGS, Cognitive/Neuropsychiatric Adverse Events subsection below).

Metabolic Acidosis:

Zonisamide causes hyperchloremic, non-anion gap, metabolic acidosis (i.e., decreased serum bicarbonate below the normal reference range in the absence of chronic respiratory alkalosis) (see PRECAUTIONS, Laboratory Testssubsection). This metabolic acidosis is caused by renal bicarbonate loss due to the inhibitory effect of zonisamide on carbonic anhydrase. Generally, zonisamide-induced metabolic acidosis occurs early in treatment, but it can develop at any time during treatment. Metabolic acidosis generally appears to be dose-dependent and can occur at doses as low as 25 mg daily.

Conditions or therapies that predispose to acidosis (such as renal disease, severe respiratory disorders, status epilepticus, diarrhea, ketogenic diet, or specific drugs) may be additive to the bicarbonate lowering effects of zonisamide.

Some manifestations of acute or chronic metabolic acidosis include hyperventilation, nonspecific symptoms such as fatigue and anorexia, or more severe sequelae including cardiac arrhythmias or stupor. Chronic, untreated, metabolic acidosis may increase the risk for nephrolithiasis or nephrocalcinosis. Nephrolithiasis has been observed in the clinical development program in 4% of adults treated with ZONEGRAN, has also been detected by renal ultrasound in 8% of pediatric treated patients who had at least one ultrasound prospectively collected, and was reported as an adverse event in 3% (4/133) of pediatric patients (see PRECAUTIONS, Kidney Stones subsection). Metabolic acidosis can also increase the risk for hyperammonemia, particularly in the presence of drugs which can cause hyperammonemia.

Chronic, untreated metabolic acidosis may result in osteomalacia (referred to as rickets in pediatric patients) and/or osteoporosis with an increased risk for fracture. Of potential relevance, zonisamide treatment was associated with reductions in serum phosphorus and increases in serum alkaline phosphatase, changes that may be related to metabolic acidosis and osteomalacia (see PRECAUTIONS, Laboratory Tests subsection).

Chronic, untreated metabolic acidosis in pediatric patients may reduce growth rates. A reduction in growth rate may eventually decrease the maximal height achieved. The effect of zonisamide on growth and bone-related sequelae has not been systematically investigated.

Measurement of baseline and periodic serum bicarbonate during treatment is recommended. If metabolic acidosis develops and persists, consideration should be given to reducing the dose or discontinuing zonisamide (using dose tapering). If the decision is made to continue patients on zonisamide in the face of persistent acidosis, alkali treatment should be considered.

Serum bicarbonate was not measured in the adjunctive controlled trials of adults with epilepsy. However, serum bicarbonate was studied in three clinical trials for indications which have not been approved: a placebo-controlled trial for migraine prophylaxis in adults, a controlled trial for monotherapy in epilepsy in adults, and an open label trial for adjunctive treatment of epilepsy in pediatric patients (3-16 years). In adults, mean serum bicarbonate reductions ranged from approximately 2 mEq/L at daily doses of 100 mg to nearly 4 mEq/L at daily doses of 300 mg. In pediatric patients, mean serum bicarbonate reductions ranged from approximately 2 mEq/L at daily doses from above 100 mg up to 300 mg, to nearly 4 mEq/L at daily doses from above 400 mg up to 600 mg.

In two controlled studies in adults, the incidence of a persistent treatment-emergent decrease in serum bicarbonate to less than 20 mEq/L (observed at 2 or more consecutive visits or the final visit) was dose-related at relatively low zonisamide doses. In the monotherapy trial of epilepsy, the incidence of a persistent treatment-emergent decrease in serum bicarbonate was 21% for daily zonisamide doses of 25 mg or 100 mg, and was 43% at a daily dose of 300 mg. In a placebo-controlled trial for prophylaxis of migraine, the incidence of a persistent treatment-emergent decrease in serum bicarbonate was 7% for placebo, 29% for 150 mg daily, and 34% for 300 mg daily. The incidence of persistent markedly abnormally low serum bicarbonate (decrease to less than 17 mEq/L and more than 5 mEq/L from a pretreatment value of at least 20 mEq/L) in these controlled trials was 2% or less.

In the pediatric study, the incidence of persistent, treatment-emergent decreases in serum bicarbonate to levels less than 20 mEq/L was 52% at doses up to 100 mg daily, was 90% for a wide range of doses up to 600 mg daily, and generally appeared to increase with higher doses. The incidence of a persistent markedly abnormally low serum bicarbonate value was 4% at doses up to 100 mg daily, was 18% for a wide range of doses up to 600 mg daily, and generally appeared to increase with higher doses. Some patients experienced moderately severe serum bicarbonate decrements down to a level as low as 10 mEq/L.

The relatively high frequencies of varying severities of metabolic acidosis observed in this study of pediatric patients (compared to the frequency and severity observed in various clinical trial development programs in adults) suggest that pediatric patients may be more likely to develop metabolic acidosis than adults.

Seizures on Withdrawal:

As with other AEDs, abrupt withdrawal of ZONEGRAN in patients with epilepsy may precipitate increased seizure frequency or status epilepticus. Dose reduction or discontinuation of zonisamide should be done gradually.

Teratogenicity:

Women of child bearing potential who are given zonisamide should be advised to use effective contraception. Zonisamide was teratogenic in mice, rats, and dogs and embryolethal in monkeys when administered during the period of organogenesis. A variety of fetal abnormalities, including cardiovascular defects, and embryo-fetal deaths occurred at maternal plasma levels similar to or lower than therapeutic levels in humans. These findings suggest that the use of ZONEGRAN during pregnancy in humans may present a significant risk to the fetus (see PRECAUTIONS, Pregnancy subsection). Zonisamide should be used during pregnancy only if the potential benefit justifies the potential risk to the fetus.

Cognitive/Neuropsychiatric Adverse Events:

Use of ZONEGRAN was frequently associated with central nervous system-related adverse events. The most significant of these can be classified into three general categories: 1) psychiatric symptoms, including depression and psychosis, 2) psychomotor slowing, difficulty with concentration, and speech or language problems, in particular, word-finding difficulties, and 3) somnolence or fatigue.

In placebo-controlled trials, 2.2% of patients discontinued ZONEGRAN or were hospitalized for depression compared to 0.4% of placebo patients. Among all epilepsy patients treated with ZONEGRAN, 1.4% were discontinued and 1.0% were hospitalized because of reported depression or suicide attempts. In placebo-controlled trials, 2.2% of patients discontinued ZONEGRAN or were hospitalized due to psychosis or psychosis-related symptoms compared to none of the placebo patients. Among all epilepsy patients treated with ZONEGRAN, 0.9% were discontinued and 1.4% were hospitalized because of reported psychosis or related symptoms.

Psychomotor slowing and difficulty with concentration occurred in the first month of treatment and were associated with doses above 300 mg/day. Speech and language problems tended to occur after 6–10 weeks of treatment and at doses above 300 mg/day. Although in most cases these events were of mild to moderate severity, they at times led to withdrawal from treatment.

Somnolence and fatigue were frequently reported CNS adverse events during clinical trials with ZONEGRAN. Although in most cases these events were of mild to moderate severity, they led to withdrawal from treatment in 0.2% of the patients enrolled in controlled trials. Somnolence and fatigue tended to occur within the first month of treatment. Somnolence and fatigue occurred most frequently at doses of 300–500 mg/day. Patients should be cautioned about this possibility and special care should be taken by patients if they drive, operate machinery, or perform any hazardous task.

Hyperammonemia and encephalopathy have been reported with the postmarketing use of zonisamide. Zonisamide treatment inhibits carbonic anhydrase activity, which may cause metabolic acidosis that is associated with an increased risk for developing hyperammonemia. Hyperammonemia resulting from zonisamide can also be asymptomatic.
The risks of hyperammonemia and various manifestations of encephalopathy may be increased in patients treated with zonisamide and concomitantly taking other medications that can cause hyperammonemia, including valproic acid or topiramate (see PRECAUTIONS). Patients with inborn errors of metabolism or reduced hepatic mitochondrial activity may be at an increased risk for hyperammonemia with or without encephalopathy and this risk may be increased by zonisamide use.
Measure serum ammonia concentration if signs or symptoms (e.g., unexplained change in mental status, vomiting, or lethargy) of encephalopathy occur. Hyperammonemia resulting from zonisamide resolves when zonisamide is discontinued. Hyperammonemia from zonisamide may resolve or decrease in severity with a decrease of the daily dose.

PRECAUTIONS

General:

Somnolence is commonly reported, especially at higher doses of ZONEGRAN (see WARNINGS: Cognitive/ Neuropsychiatric Adverse Events subsection). Zonisamide is metabolized by the liver and eliminated by the kidneys; caution should therefore be exercised when administering ZONEGRAN to patients with hepatic and renal dysfunction (see CLINICAL PHARMACOLOGY, Specific Populations subsection).

Kidney Stones:

Among 991 patients treated during the development of ZONEGRAN, 40 patients (4.0%) with epilepsy receiving ZONEGRAN developed clinically possible or confirmed kidney stones (e.g., clinical symptomatology, sonography, etc.), a rate of 34 per 1000 patient-years of exposure (40 patients with 1168 years of exposure). Of these, 12 were symptomatic, and 28 were described as possible kidney stones based on sonographic detection. In nine patients, the diagnosis was confirmed by a passage of a stone or by a definitive sonographic finding. The rate of occurrence of kidney stones was 28.7 per 1000 patient-years of exposure in the first six months, 62.6 per 1000 patient-years of exposure between 6 and 12 months, and 24.3 per 1000 patient-years of exposure after 12 months of use. There are no normative sonographic data available for either the general population or patients with epilepsy. Although the clinical significance of the sonographic findings may not be certain, the development of nephrolithiasis may be related to metabolic acidosis (see WARNINGS, Metabolic Acidosis subsection). The analyzed stones were composed of calcium or urate salts. In general, increasing fluid intake and urine output can help reduce the risk of stone formation, particularly in those with predisposing risk factors. It is unknown, however, whether these measures will reduce the risk of stone formation in patients treated with ZONEGRAN.

Although not approved in pediatric patients, sonographic findings consistent with nephrolithiasis were also detected in 8% of a subset of ZONEGRAN treated pediatric patients who had at least one renal ultrasound prospectively performed in a clinical development program investigating open-label treatment. The incidence of kidney stone as an adverse event was 3% (see WARNINGS, Metabolic Acidosis subsection).

Effect on Renal Function:

In several clinical studies, zonisamide was associated with a statistically significant 8% mean increase from baseline of serum creatinine and blood urea nitrogen (BUN) compared to essentially no change in the placebo patients. The increase appeared to persist over time but was not progressive; this has been interpreted as an effect on glomerular filtration rate (GFR). There were no episodes of unexplained acute renal failure in clinical development in the US, Europe, or Japan. The decrease in GFR appeared within the first 4 weeks of treatment. In a 30-day study, the GFR returned to baseline within 2–3 weeks of drug discontinuation. There is no information about reversibility, after drug discontinuation, of the effects on GFR after long-term use. ZONEGRAN should be discontinued in patients who develop acute renal failure or a clinically significant sustained increase in the creatinine/BUN concentration. ZONEGRAN should not be used in patients with renal failure (estimated GFR < 50 mL/min) as there has been insufficient experience concerning drug dosing and toxicity.

Status Epilepticus:

Estimates of the incidence of treatment emergent status epilepticus in ZONEGRAN treated patients are difficult because a standard definition was not employed. Nonetheless, in controlled trials, 1.1% of patients treated with ZONEGRAN had an event labeled as status epilepticus compared to none of the patients treated with placebo. Among patients treated with ZONEGRAN across all epilepsy studies (controlled and uncontrolled), 1.0% of patients had an event reported as status epilepticus.

Information for Patients:

Inform patients of the availability of a Medication Guide, and instruct them to read the Medication Guide prior to taking ZONEGRAN. Instruct patients to take ZONEGRAN only as prescribed.

Advise patients as follows: (See Medication Guide)

1. ZONEGRAN may produce drowsiness, especially at higher doses. Patients should be advised not to drive a car or operate other complex machinery until they have gained experience on ZONEGRAN sufficient to determine whether it affects their performance. Because of the potential of zonisamide to cause CNS depression, as well as other cognitive and/or neuropsychiatric adverse events, ZONEGRAN should be used with caution if used in combination with alcohol or other CNS depressants.
2. Patients should contact their physicians immediately if a skin rash develops (see WARNINGS, Serious Skin Reactions subsection).
3. Instruct patients to seek immediate medical attention if they experience blurred vision, visual disturbances, or periorbital pain (see WARNINGS, Acute Myopia and Secondary Angle Closure Glaucoma subsection).
4. Patients should contact their physician immediately if they develop signs or symptoms, such as sudden back pain, abdominal pain, and/or blood in the urine, that could indicate a kidney stone. Increasing fluid intake and urine output may reduce the risk of stone formation, particularly in those with predisposing risk factors for stones (see PRECAUTIONS, Kidney Stones subsection).
5. Patients should contact their physician immediately if a child has been taking ZONEGRAN and is not sweating as usual with or without a fever (see WARNINGS, Oligohidrosis and Hyperthermia in Pediatric Patients subsection).
6. Because zonisamide can cause hematological complications, patients should contact their physician immediately if they develop a fever, sore throat, oral ulcers, or easy bruising (see WARNINGS, Serious Hematologic Events subsection).
7. Counsel patients and caregivers that AEDs, including ZONEGRAN, may increase the risk of suicidal thoughts and behavior and advise them of the need to be alert for the emergence or worsening of symptoms of depression, any unusual changes in mood or behavior, or the emergence of suicidal thoughts, behavior, or thoughts about self-harm. Behaviors of concern should be reported immediately to healthcare providers (see WARNINGS, Suicidal Behavior and Ideation subsection).
8. Warn patients about the possible development of hyperammonemia with or without encephalopathy. Although hyperammonemia may be asymptomatic, clinical symptoms of hyperammonemic encephalopathy often include acute alterations in level of consciousness and/or cognitive function with lethargy and/or vomiting. Instruct patients to contact their physician if they develop unexplained lethargy, vomiting, or changes in mental status (see WARNINGS, Hyperammonemia and Encephalopathy subsection).
9. Patients should contact their physician immediately if they develop fast breathing, fatigue/tiredness, loss of appetite, or irregular heart beat or palpitations, which are possible manifestations of metabolic acidosis (see WARNINGS, Metabolic Acidosis subsection).
10. As with other AEDs, patients should contact their physician if they intend to become pregnant or are pregnant during ZONEGRAN therapy. Patients should notify their physician if they intend to breast-feed or are breast-feeding an infant (see PRECAUTIONS, Use in Nursing Mothers subsection).
11. Encourage patients to enroll in the North American Antiepileptic Drug (NAAED) Pregnancy Registry if they become pregnant. This registry is collecting information about the safety of antiepileptic drugs during pregnancy. To enroll, patients can call the toll-free number 1-888-233-2334 (see PRECAUTIONS, Pregnancy subsection).

Laboratory Tests:

In several clinical studies, zonisamide was associated with a mean increase in the concentration of serum creatinine and blood urea nitrogen (BUN) of approximately 8% over the baseline measurement. Consideration should be given to monitoring renal function periodically (see PRECAUTIONS, Effect on Renal Function subsection).

Zonisamide increases serum chloride and alkaline phosphatase and decreases serum bicarbonate (see WARNINGS, Metabolic Acidosis subsection), phosphorus, calcium, and albumin.

DRUG INTERACTIONS

Drug Interactions with CNS Depressants: Concomitant administration of ZONEGRAN and alcohol or other CNS depressant drugs has not been evaluated in clinical studies. Because of the potential of zonisamide to cause CNS depression, as well as other cognitive and/or neuropsychiatric adverse events, zonisamide should be used with caution if used in combination with alcohol or other CNS depressants.

Other Carbonic Anhydrase Inhibitors: Concomitant use of ZONEGRAN, a carbonic anhydrase inhibitor, with any other carbonic anhydrase inhibitor (e.g., topiramate, acetazolamide or dichlorphenamide), may increase the severity of metabolic acidosis and may also increase the risk of kidney stone formation or the risk of hyperammonemia. Therefore, if ZONEGRAN is given concomitantly with another carbonic anhydrase inhibitor, the patient should be monitored for the appearance or worsening of metabolic acidosis (see CLINICAL PHARMACOLOGY, Interactions of Zonisamide with Other Carbonic Anhydrase Inhibitors subsection and WARNINGS, Metabolic Acidosis subsection and Hyperammonemia and Encephalopathy subsection).

Carcinogenicity, Mutagenesis, Impairment of Fertility:

No evidence of carcinogenicity was found in mice or rats following dietary administration of zonisamide for two years at doses of up to 80 mg/kg/day. In mice, this dose is approximately equivalent to the maximum recommended human dose (MRHD) of 400 mg/day on a mg/m^2 basis. In rats, this dose is 1–2 times the MRHD on a mg/m^2 basis.

Zonisamide was mutagenic in an in vitro chromosomal aberration assay in CHL cells. Zonisamide was not mutagenic or clastogenic in other in vitro assays (Ames, mouse lymphoma tk assay, chromosomal aberration in human lymphocytes) or in the in vivo rat bone marrow cytogenetics assay.

Rats treated with zonisamide (20, 60, or 200 mg/kg) before mating and during the initial gestation phase showed signs of reproductive toxicity (decreased corpora lutea, implantations, and live fetuses) at all doses. The low dose in this study is approximately 0.5 times the maximum recommended human dose (MRHD) on a mg/m^2 basis.

Pregnancy: (see WARNINGS, Teratogenicity subsection):

Zonisamide may cause serious adverse fetal effects, based on clinical and nonclinical data. Zonisamide was teratogenic in multiple animal species.

Zonisamide treatment causes metabolic acidosis in humans. The effect of zonisamide-induced metabolic acidosis has not been studied in pregnancy; however, metabolic acidosis in pregnancy (due to other causes) may be associated with decreased fetal growth, decreased fetal oxygenation, and fetal death, and may affect the fetus's ability to tolerate labor. Pregnant patients should be monitored for metabolic acidosis and treated as in the non-pregnant state. (See WARNINGS, Metabolic Acidosis subsection.)

Newborns of mothers treated with zonisamide should be monitored for metabolic acidosis because of transfer of zonisamide to the fetus and possible occurrence of transient metabolic acidosis following birth. Transient metabolic acidosis has been reported in neonates born to mothers treated during pregnancy with a different carbonic anhydrase inhibitor.

Zonisamide was teratogenic in mice, rats, and dogs and embryolethal in monkeys when administered during the period of organogenesis. Fetal abnormalities or embryo-fetal deaths occurred in these species at zonisamide dosage and maternal plasma levels similar to or lower than therapeutic levels in humans, indicating that use of this drug in pregnancy entails a significant risk to the fetus. A variety of external, visceral, and skeletal malformations was produced in animals by prenatal exposure to zonisamide. Cardiovascular defects were prominent in both rats and dogs.

Following administration of zonisamide (10, 30, or 60 mg/kg/day) to pregnant dogs during organogenesis, increased incidences of fetal cardiovascular malformations (ventricular septal defects, cardiomegaly, various valvular and arterial anomalies) were found at doses of 30 mg/kg/day or greater. The low effect dose for malformations produced peak maternal plasma zonisamide levels (25 μg/mL) about 0.5 times the highest plasma levels measured in patients receiving the maximum recommended human dose (MRHD) of 400 mg/day. In dogs, cardiovascular malformations were found in approximately 50% of all fetuses exposed to the high dose, which was associated with maternal plasma levels (44 μg/mL) approximately equal to the highest levels measured in humans receiving the MRHD. Incidences of skeletal malformations were also increased at the high dose, and fetal growth retardation and increased frequencies of skeletal variations were seen at all doses in this study. The low dose produced maternal plasma levels (12 μg/mL) about 0.25 times the highest human levels.

In cynomolgus monkeys, administration of zonisamide (10 or 20 mg/kg/day) to pregnant animals during organogenesis resulted in embryo-fetal deaths at both doses. The possibility that these deaths were due to malformations cannot be ruled out. The lowest embryolethal dose in monkeys was associated with peak maternal plasma zonisamide levels (5 μg/mL) approximately 0.1 times the highest levels measured in patients at the MRHD.

In a mouse embryo-fetal development study, treatment of pregnant animals with zonisamide (125, 250, or 500 mg/kg/day) during the period of organogenesis resulted in increased incidences of fetal malformations (skeletal and/or craniofacial defects) at all doses tested. The low dose in this study is approximately 1.5 times the MRHD on a mg/m^2 basis. In rats, increased frequencies of malformations (cardiovascular defects) and variations (persistent cords of thymic tissue, decreased skeletal ossification) were observed among the offspring of dams treated with zonisamide (20, 60, or 200 mg/kg/day) throughout organogenesis at all doses. The low effect dose is approximately 0.5 times the MRHD on a mg/m^2 basis.

Perinatal death was increased among the offspring of rats treated with zonisamide (10, 30, or 60 mg/kg/day) from the latter part of gestation up to weaning at the high dose, or approximately 1.4 times the MRHD on a mg/m^2 basis. The no effect level of 30 mg/kg/day is approximately 0.7 times the MRHD on a mg/m^2 basis.

There are no adequate and well-controlled studies in pregnant women. ZONEGRAN should be used during pregnancy only if the potential benefit justifies the potential risk to the fetus.

To provide information regarding the effects of in utero exposure to ZONEGRAN, physicians are advised to recommend that pregnant patients taking ZONEGRAN enroll in the NAAED Pregnancy Registry. This can be done by calling the toll free number 1-888-233-2334, and must be done by patients themselves. Information on the registry can also be found at the website http://www.aedpregnancyregistry.org/.

Labor and Delivery:

The effects of ZONEGRAN on labor and delivery in humans are unknown.

Use in Nursing Mothers:

Zonisamide is excreted in human milk. Because of the potential for serious adverse reactions in nursing infants from ZONEGRAN, a decision should be made whether to discontinue nursing or to discontinue drug, taking into account the importance of the drug to the mother.

Pediatric Use:

The safety and effectiveness of ZONEGRAN in children under age 16 have not been established. Acute myopia and secondary angle closure glaucoma have been reported in pediatric patients (see WARNINGS, Acute Myopia and Secondary Angle Closure Glaucoma subsection). Cases of oligohidrosis and hyperpyrexia have been reported (see WARNINGS, Oligohidrosis and Hyperthermia in Pediatric Patients subsection). Zonisamide commonly causes metabolic acidosis in pediatric patients (see WARNINGS, Metabolic Acidosis subsection). Hyperammonemia with encephalopathy has been reported in pediatric patients (see WARNINGS, Hyperammonemia and Encephalopathy subsection). Chronic untreated metabolic acidosis in pediatric patients may cause nephrolithiasis and/or nephrocalcinosis, osteoporosis and/or osteomalacia (potentially resulting in rickets), and may reduce growth rates. A reduction in growth rate may eventually decrease the maximal height achieved. The effect of zonisamide on growth and bone-related sequelae has not been systematically investigated.

Geriatric Use:

Single dose pharmacokinetic parameters are similar in elderly and young healthy volunteers (see CLINICAL PHARMACOLOGY, Specific Populations subsection). Clinical studies of zonisamide did not include sufficient numbers of subjects aged 65 and over to determine whether they respond differently from younger subjects. Other reported clinical experience has not identified differences in responses between the elderly and younger patients. In general, dose selection for an elderly patient should be cautious, usually starting at the low end of the dosing range, reflecting the greater frequency of decreased hepatic, renal, or cardiac function, and of concomitant disease or other drug therapy.

ADVERSE REACTIONS

The most common adverse reactions with ZONEGRAN (an incidence at least 4% greater than placebo) in controlled clinical trials and shown in descending order of frequency were somnolence, anorexia, dizziness, ataxia, agitation/irritability, and difficulty with memory and/or concentration.

In controlled clinical trials, 12% of patients receiving ZONEGRAN as adjunctive therapy discontinued due to an adverse reaction compared to 6% receiving placebo. Approximately 21% of the 1,336 patients with epilepsy who received ZONEGRAN in clinical studies discontinued treatment because of an adverse reaction. The most common adverse reactions leading to discontinuation were somnolence, fatigue and/or ataxia (6%), anorexia (3%), difficulty concentrating (2%), difficulty with memory, mental slowing, nausea/vomiting (2%), and weight loss (1%). Many of these adverse reactions were dose-related (see WARNINGS and PRECAUTIONS).

Adverse Reaction Incidence in Controlled Clinical Trials:

Table 4 lists adverse reactions that occurred in at least 2% of patients treated with ZONEGRAN in controlled clinical trials that were numerically more common in the ZONEGRAN group. In these studies, either ZONEGRAN or placebo was added to the patient's current AED therapy.

Table 4. Adverse Reactions in Placebo-Controlled, Add-On Trials (Events that occurred in at least 2% of ZONEGRAN-treated patients and occurred more frequently in ZONEGRAN-treated than placebo-treated patients)
BODY SYSTEM/PREFERRED TERM | ZONEGRAN (n=269) % | PLACEBO (n=230) %
BODY AS A WHOLE
Headache | 10 | 8
Abdominal Pain | 6 | 3
Flu Syndrome | 4 | 3
DIGESTIVE
Anorexia | 13 | 6
Nausea | 9 | 6
Diarrhea | 5 | 2
Dyspepsia | 3 | 1
Constipation | 2 | 1
Dry Mouth | 2 | 1
HEMATOLOGIC AND LYMPHATIC
Ecchymosis | 2 | 1
METABOLIC AND NUTRITIONAL
Weight Loss | 3 | 2
NERVOUS SYSTEM
Dizziness | 13 | 7
Ataxia | 6 | 1
Nystagmus | 4 | 2
Paresthesia | 4 | 1
NEUROPSYCHIATRIC AND COGNITIVE DYSFUNCTION-ALTERED COGNITIVE FUNCTION
Confusion | 6 | 3
Difficulty Concentrating | 6 | 2
Difficulty with Memory | 6 | 2
Mental Slowing | 4 | 2
NEUROPSYCHIATRIC AND COGNITIVE DYSFUNCTION-BEHAVIORAL ABNORMALITIES (NON-PSYCHOSIS-RELATED)
Agitation/Irritability | 9 | 4
Depression | 6 | 3
Insomnia | 6 | 3
Anxiety | 3 | 2
Nervousness | 2 | 1
NEUROPSYCHIATRIC AND COGNITIVE DYSFUNCTION-BEHAVIORAL ABNORMALITIES (PSYCHOSIS-RELATED)
Schizophrenic/Schizophreniform Behavior | 2 | 0
NEUROPSYCHIATRIC AND COGNITIVE DYSFUNCTION-CNS DEPRESSION
Somnolence | 17 | 7
Fatigue | 8 | 6
Tiredness | 7 | 5
NEUROPSYCHIATRIC AND COGNITIVE DYSFUNCTION-SPEECH AND LANGUAGE ABNORMALITIES
Speech Abnormalities | 5 | 2
Difficulties in Verbal Expression | 2 | <1
RESPIRATORY
Rhinitis | 2 | 1
SKIN AND APPENDAGES
Rash | 3 | 2
SPECIAL SENSES
Diplopia | 6 | 3
Taste Perversion | 2 | 0

Other Adverse Reactions in Clinical Trials:

ZONEGRAN has been administered to 1,598 individuals during all clinical trials, only some of which were placebo-controlled. The frequencies represent the proportion of the 1,598 individuals exposed to ZONEGRAN who experienced an event on at least one occasion. All events are included except those already listed in the previous table or discussed in WARNINGS or PRECAUTIONS, trivial events, those too general to be informative, and those not reasonably associated with ZONEGRAN.

Events are further classified within each category and listed in order of decreasing frequency as follows: frequent occurring in at least 1:100 patients; infrequent occurring in 1:100 to 1:1000 patients; rare occurring in fewer than 1:1000 patients.

Body as a Whole: Frequent: Accidental injury, asthenia. Infrequent: Chest pain, flank pain, malaise, allergic reaction, face edema, neck rigidity. Rare: Lupus erythematosus.

Cardiovascular: Infrequent: Palpitation, tachycardia, vascular insufficiency, hypotension, hypertension, thrombophlebitis, syncope, bradycardia. Rare: Atrial fibrillation, heart failure, pulmonary embolus, ventricular extrasystoles.

Digestive: Frequent: Vomiting. Infrequent: Flatulence, gingivitis, gum hyperplasia, gastritis, gastroenteritis, stomatitis, cholelithiasis, glossitis, melena, rectal hemorrhage, ulcerative stomatitis, gastro-duodenal ulcer, dysphagia, gum hemorrhage. Rare: Cholangitis, hematemesis, cholecystitis, cholestatic jaundice, colitis, duodenitis, esophagitis, fecal incontinence, mouth ulceration.

Hematologic and Lymphatic: Infrequent: Leukopenia, anemia, immunodeficiency, lymphadenopathy. Rare: Thrombocytopenia, microcytic anemia, petechia.

Metabolic and Nutritional: Infrequent: Peripheral edema, weight gain, edema, thirst, dehydration. Rare: Hypoglycemia, hyponatremia, lactic dehydrogenase increased, SGOT increased, SGPT increased.

Musculoskeletal: Infrequent: Leg cramps, myalgia, myasthenia, arthralgia, arthritis.

Nervous System: Frequent: Tremor, convulsion, abnormal gait, hyperesthesia, incoordination. Infrequent: Hypertonia, twitching, abnormal dreams, vertigo, libido decreased, neuropathy, hyperkinesia, movement disorder, dysarthria, cerebrovascular accident, hypotonia, peripheral neuritis, reflexes increased. Rare: Dyskinesia, dystonia, encephalopathy, facial paralysis, hypokinesia, hyperesthesia, myoclonus, oculogyric crisis.

Behavioral Abnormalities –Non-Psychosis-Related: Infrequent: Euphoria.

Respiratory: Frequent: Pharyngitis, cough increased. Infrequent: Dyspnea. Rare: Apnea, hemoptysis.

Skin and Appendages: Frequent: Pruritus. Infrequent: Maculopapular rash, acne, alopecia, dry skin, sweating, eczema, urticaria, hirsutism, pustular rash, vesiculobullous rash.

Special Senses: Frequent: Amblyopia, tinnitus. Infrequent: Conjunctivitis, parosmia, deafness, visual field defect, glaucoma. Rare: Photophobia, iritis.

Urogenital: Infrequent: Urinary frequency, dysuria, urinary incontinence, hematuria, impotence, urinary retention, urinary urgency, amenorrhea, polyuria, nocturia. Rare: Albuminuria, enuresis, bladder pain, bladder calculus, gynecomastia, mastitis, menorrhagia.

POST MARKETING EXPERIENCE

The following serious adverse reactions have been reported since approval and use of ZONEGRAN worldwide. These reactions are reported voluntarily from a population of uncertain size; therefore, it is not possible to estimate their frequency or establish a causal relationship to drug exposure.

Acute pancreatitis, rhabdomyolysis, increased creatine phosphokinase, drug reaction with eosinophilia and systemic symptoms (DRESS), acute myopia and secondary angle closure glaucoma, and hyperammonemia and encephalopathy (see WARNINGS).

To report SUSPECTED ADVERSE REACTIONS, contact Advanz Pharma (US) Corp. at 1-877-370-1142 or the FDA at 1-800-FDA-1088
or www.fda.gov/medwatch.

DRUG ABUSE AND DEPENDENCE

The abuse and dependence potential of ZONEGRAN has not been evaluated in human studies (see WARNINGS, Cognitive/Neuropsychiatric Adverse Events subsection). In a series of animal studies, zonisamide did not demonstrate abuse liability and dependence potential. Monkeys did not self-administer zonisamide in a standard reinforcing paradigm. Rats exposed to zonisamide did not exhibit signs of physical dependence of the CNS-depressant type. Rats did not generalize the effects of diazepam to zonisamide in a standard discrimination paradigm after training, suggesting that zonisamide does not have abuse potential of the benzodiazepine-CNS depressant type.

OVERDOSAGE

Human Experience:

Experience with ZONEGRAN daily doses over 800 mg/day is limited. During ZONEGRAN clinical development, three patients ingested unknown amounts of ZONEGRAN as suicide attempts, and all three were hospitalized with CNS symptoms. One patient became comatose and developed bradycardia, hypotension, and respiratory depression; the zonisamide plasma level was 100.1 μg/mL measured 31 hours post-ingestion. Zonisamide plasma levels fell with a half-life of 57 hours, and the patient became alert five days later.

Management:

No specific antidotes for ZONEGRAN overdosage are available. Following a suspected recent overdose, emesis should be induced or gastric lavage performed with the usual precautions to protect the airway. General supportive care is indicated, including frequent monitoring of vital signs and close observation.

Zonisamide has a long half-life (see CLINICAL PHARMACOLOGY section). Due to the low protein binding of zonisamide (40%), renal dialysis may be effective. The effectiveness of renal dialysis as a treatment of overdose has not been formally studied. A poison control center should be contacted for information on the management of ZONEGRAN overdosage.

DOSAGE AND ADMINISTRATION

ZONEGRAN (zonisamide) is recommended as adjunctive therapy for the treatment of partial seizures in adults. Safety and efficacy in pediatric patients below the age of 16 have not been established. ZONEGRAN should be administered once or twice daily, using 25 mg or 100 mg capsules. ZONEGRAN is given orally and can be taken with or without food. Capsules should be swallowed whole.

Adults over Age 16:

The prescriber should be aware that, because of the long half-life of zonisamide, up to two weeks may be required to achieve steady state levels upon reaching a stable dose or following dosage adjustment. Although the regimen described below is one that has been shown to be tolerated, the prescriber may wish to prolong the duration of treatment at the lower doses in order to fully assess the effects of zonisamide at steady state, noting that many of the side effects of zonisamide are more frequent at doses of 300 mg per day and above. Although there is some evidence of greater response at doses above 100–200 mg/day, the increase appears small and formal dose-response studies have not been conducted.

The initial dose of ZONEGRAN should be 100 mg daily. After two weeks, the dose may be increased to 200 mg/day for at least two weeks. It can be increased to 300 mg/day and 400 mg/day, with the dose stable for at least two weeks to achieve steady state at each level. Evidence from controlled trials suggests that ZONEGRAN doses of 100–600 mg/day are effective, but there is no suggestion of increasing response above 400 mg/day (see CLINICAL PHARMACOLOGY, Clinical Studies subsection). There is little experience with doses greater than 600 mg/day.

Patients with Renal or Hepatic Disease:

Because zonisamide is metabolized in the liver and excreted by the kidneys, patients with renal or hepatic disease should be treated with caution, and might require slower titration and more frequent monitoring (see CLINICAL PHARMACOLOGY and PRECAUTIONS).

HOW SUPPLIED

ZONEGRAN is available as 25 mg and 100 mg two-piece hard gelatin capsules. The capsules are printed in black with “ZONEGRAN 25” or “ZONEGRAN 100,” respectively. ZONEGRAN is available in bottles of 100 with strengths and colors as follows:

Dosage Strength | Capsule Colors | NDC #
25 mg | White opaque body with white opaque cap. | 59212-681-10
100 mg | White opaque body with red opaque cap. | 59212-680-10

Store at 25°C (77°F), excursions permitted to 15–30°C (59–86°F) [see USP Controlled Room Temperature], in a dry place and protected from light.

Manufactured for:
Advanz Pharma (US) Corp.
Bannockburn, IL 60015

ZONEGRAN® is a registered trademark of Mercury Pharma Group Limited in the United States and Puerto Rico.
Distributed by Advanz Pharma (US) Corp. under license.

Revised: 11/2023

Medication Guide

ZONEGRAN® (ZO-nuh-gran)

(zonisamide) capsules

What is the most important information I should know about ZONEGRAN?

ZONEGRAN may cause serious side effects, including:

1. Serious skin rash that can cause death.
2. Serious allergic reactions that may affect different parts of the body.
3. Less sweating and increase in your body temperature (fever).
4. Serious eye problems
5. Suicidal thoughts or actions in some people.
6. Increased level of acid in your blood (metabolic acidosis).
7. Problems with your concentration, attention, memory, thinking, speech, or language.
8. Blood cell changes such as reduced red and white blood cell counts.

These serious side effects are described below.

1. ZONEGRAN may cause a serious skin rash that can cause death. These serious skin reactions are more likely to happen when you begin taking ZONEGRAN within the first 4 months of treatment but may occur at later times.
2. ZONEGRAN can cause other types of allergic reactions or serious problems that may affect different parts of the body such as your liver, kidneys, heart, or blood cells. You may or may not have a rash with these types of reactions. These reactions can be very serious and can cause death. Call your health care provider right away if you have:
  - fever
  - severe muscle pain
  - rash
  - swollen lymph glands
  - swelling of your face
  - unusual bruising or bleeding
  - weakness, fatigue
  - yellowing of your skin or the white part of your eyes
3. ZONEGRAN may cause you to sweat less and to increase your body temperature (fever). You may need to be hospitalized for this. You should watch for decreased sweating and fever, especially when it is hot and especially in children taking ZONEGRAN.
  Call your health care provider right away if you have:
  - high fever, recurring fever, or long lasting fever
  - less sweat than normal
4. ZONEGRAN may cause eye problems. Serious eye problems include:
  • sudden decrease in vision with or without eye pain and redness
  • a blockage of fluid in the eye causing increased pressure in the eye (secondary angle closure glaucoma)
  These eye problems can lead to permanent loss of vision if not treated.
  Call your healthcare provider right away if you have any new eye symptoms, including any eye pain or redness or any new problems with your vision.
5. Like other antiepileptic drugs, ZONEGRAN may cause suicidal thoughts or actions in a very small number of people, about 1 in 500.
  Call a healthcare provider right away if you have any of these symptoms, especially if they are new, worse, or worry you:
  - thoughts about suicide or dying
  - attempt to commit suicide
  - new or worse depression
  - new or worse anxiety
  - feeling agitated or restless
  - panic attacks
  - trouble sleeping (insomnia)
  - new or worse irritability
  - acting aggressive, being angry, or violent
  - acting on dangerous impulses
  - an extreme increase in activity and talking (mania)
  - other unusual changes in behavior or mood
  - Suicidal thoughts or actions can be caused by things other than medicines. If you have suicidal thoughts or actions, your healthcare provider may check for other causes.
  How can I watch for early symptoms of suicidal thoughts and actions?
  - Pay attention to any changes, especially sudden changes, in mood, behaviors, thoughts, or feelings.
  - Keep all follow-up visits with your healthcare provider as scheduled.
  Call your healthcare provider between visits as needed, especially if you are worried about symptoms.
  Do not stop ZONEGRAN without first talking to a healthcare provider.
  Stopping ZONEGRAN suddenly can cause serious problems. Stopping a seizure medicine suddenly in a patient who has epilepsy can cause seizures that will not stop (status epilepticus).
6. ZONEGRAN can increase the level of acid in your blood (metabolic acidosis). If left untreated, metabolic acidosis can cause brittle or soft bones (osteoporosis, osteomalacia, osteopenia), kidney stones and can slow the rate of growth in children. Metabolic acidosis can happen with or without symptoms.
  Sometimes people with metabolic acidosis will:
  - feel tired
  - not feel hungry (loss of appetite)
  - feel changes in heartbeat
  - have trouble thinking clearly
  Your healthcare provider should do a blood test to measure the level of acid in your blood before and during your treatment with ZONEGRAN.
7. ZONEGRAN may cause problems with your concentration, attention, memory, thinking, speech, or language.
8. ZONEGRAN can cause blood cell changes such as reduced red and white blood cell counts. Call your healthcare provider if you develop fever, sore throat, sores in your mouth, or unusual bruising.

ZONEGRAN can have other serious side effects. For more information ask your healthcare provider or pharmacist. Tell your healthcare provider if you have any side effect that bothers you. Be sure to read the section titled "What are the possible side effects of ZONEGRAN?"

What is ZONEGRAN?
ZONEGRAN is a prescription medicine that is used with other medicines to treat partial seizures in adults.
It is not known if ZONEGRAN is safe or effective in children under 16 years of age.
Do not take ZONEGRAN:
Do not take ZONEGRAN if you are allergic to medicines that contain sulfa.
Before taking ZONEGRAN, tell your healthcare provider about all your medical conditions, including if you:

- have or have had depression, mood problems or suicidal thoughts or behavior
- have kidney problems
- have liver problems
- have a history of metabolic acidosis (too much acid in your blood)
- have weak, brittle bones or soft bones (osteomalacia, osteopenia or osteoporosis)
- have a growth problem
- are on a diet high in fat called a ketogenic diet
- have diarrhea
- have high blood levels of ammonia

Tell your healthcare provider if you:

- are pregnant or plan to become pregnant. ZONEGRAN may harm your unborn baby. Women who can become pregnant should use effective birth control. Tell your healthcare provider right away if you become pregnant while taking ZONEGRAN.
  You and your healthcare provider should decide if you should take ZONEGRAN while you are pregnant.
  If you become pregnant while taking ZONEGRAN, talk to your healthcare provider about registering with the North American Antiepileptic Drug Pregnancy Registry. You can enroll in this registry by calling 1-888-233-2334. The purpose of this registry is to collect information about the safety of antiepileptic drugs during pregnancy.
- are breastfeeding or plan to breastfeed. ZONEGRAN can pass into your breast milk. It is not known if ZONEGRAN in your breast milk can harm your baby. Talk to your healthcare provider about the best way to feed your baby if you take ZONEGRAN.

Tell your healthcare provider about all the medicines you take, including prescription and over-the-counter medicines, vitamins and herbal supplements.

How should I take ZONEGRAN?

- Take ZONEGRAN exactly as prescribed. Your healthcare prescriber may change your dose. Your healthcare provider will tell you how much ZONEGRAN to take.
- Take ZONEGRAN with or without food.
- Swallow the capsules whole.
- If you take too much ZONEGRAN, call your local Poison Control Center or go to the nearest emergency room right away.
- Do not stop taking ZONEGRAN without talking to your healthcare provider. Stopping ZONEGRAN suddenly can cause serious problems, including seizures that will not stop (status epilepticus).

What should I avoid while taking ZONEGRAN?

- Do not drink alcohol or take other drugs that make you sleepy or dizzy while taking ZONEGRAN until you talk to your health care provider. ZONEGRAN taken with alcohol or drugs that cause sleepiness or dizziness may make your sleepiness or dizziness worse.
- Do not drive, operate heavy machinery, or do other dangerous activities until you know how ZONEGRAN affects you. ZONEGRAN can slow your thinking and motor skills.

What are the possible side effects of ZONEGRAN?

ZONEGRAN can cause serious side effects. See "What is the most important information I should know about ZONEGRAN?"

Other serious side effects include:

- kidney stones. Back pain, stomach pain, or blood in your urine may mean you have kidney stones. Drink plenty of fluids while you take ZONEGRAN to lower your chance of getting kidney stones.
- problems with mood or thinking (new or worse depression; sudden changes in mood, behavior, or loss of contact with reality, sometimes associated with hearing voices or seeing things that are not really there; feeling sleepy or tired; trouble concentrating; speech and language problems). Call your healthcare provider right away if you have any of the symptoms listed above.
- high blood ammonia levels. High ammonia in the blood can affect your mental activities, slow your alertness, make you feel tired, or cause vomiting.

The most common side effects of ZONEGRAN include:

- drowsiness
- loss of appetite
- dizziness
- problems with concentration or memory
- trouble with walking and coordination
- agitation or irritability

Side effects can happen at any time, but are more likely to happen during the first several weeks after starting ZONEGRAN.

These are not all of the possible side effects of ZONEGRAN. Call your doctor for medical advice about side effects. You may report side effects to FDA at 1-800-FDA-1088.

How should I store ZONEGRAN?

- Store ZONEGRAN between 59°F to 86°F (15°C to 30°C)
- Keep ZONEGRAN dry and away from light

Keep ZONEGRAN and all medicines out of the reach of children.

General Information about the safe and effective use of ZONEGRAN

Medicines are sometimes prescribed for purposes other than those listed in a Medication Guide. Do not use ZONEGRAN for a condition for which it was not prescribed. Do not give ZONEGRAN to other people, even if they have the same symptoms that you have. It may harm them. You can ask your pharmacist or healthcare provider for information about ZONEGRAN that is written for health professionals.

What are the ingredients in ZONEGRAN?

Active ingredient: zonisamide

Inactive ingredients in ZONEGRAN 25 mg capsules: microcrystalline cellulose, hydrogenated vegetable oil, sodium lauryl sulfate, gelatin, and titanium dioxide

Inactive ingredients in ZONEGRAN 100 mg capsules: microcrystalline cellulose, hydrogenated vegetable oil, sodium lauryl sulfate, gelatin, and titanium dioxide, FD&C Red No. 40 and FD&C Yellow No. 6

Manufactured for:
Advanz Pharma (US) Corp.
Bannockburn, IL 60015

ZONEGRAN® is a registered trademark of Mercury Pharma Group Limited in the United States and Puerto Rico.
Distributed by Advanz Pharma (US) Corp. under license.

This Medication Guide has been approved by the U.S. Food and Drug Administration.

Revised: November 2023

PACKAGE LABEL

PRINCIPAL DISPLAY PANEL - 25 mg Capsules

NDC 59212-681-10

Zonegran®
(zonisamide) capsules
25 mg 100 capsules

Rx only

Dispense accompanying Medication Guide to each patient.

Mfd. for:ADVANZ PHARMA

PACKAGE LABEL

PRINCIPAL DISPLAY PANEL - 100 mg Capsules

NDC 59212-680-10

Zonegran®
(zonisamide) capsules
100 mg 100 capsules

Rx only

Dispense accompanying Medication Guide to each patient.

Mfd. for:ADVANZ PHARMA